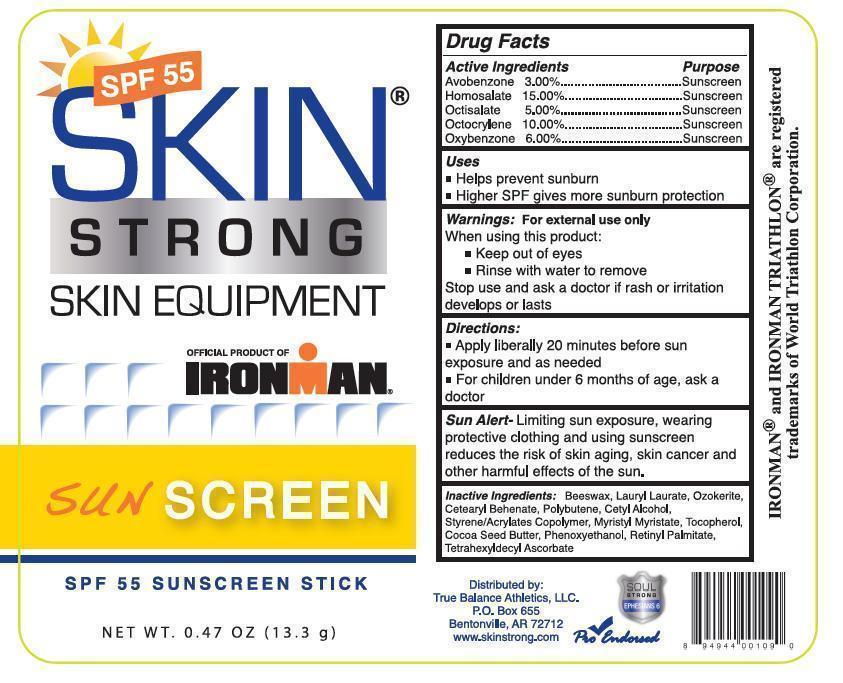 DRUG LABEL: SKIN STRONG - SKIN EQUIPMENT
NDC: 51401-002 | Form: STICK
Manufacturer: True Balance Athletics LLC
Category: otc | Type: HUMAN OTC DRUG LABEL
Date: 20121219

ACTIVE INGREDIENTS: AVOBENZONE 30 mg/1 g; HOMOSALATE 150 mg/1 g; OCTISALATE 50 mg/1 g; OCTOCRYLENE 100 mg/1 g; OXYBENZONE 60 mg/1 g
INACTIVE INGREDIENTS: YELLOW WAX; LAURYL LAURATE; CERESIN; CETEARYL BEHENATE; POLYBUTENE (1400 MW); CETYL ALCOHOL; MYRISTYL MYRISTATE; TOCOPHEROL; COCOA BUTTER; PHENOXYETHANOL; VITAMIN A PALMITATE; TETRAHEXYLDECYL ASCORBATE

SKIN STRONG SKIN EQUIPMENT - SPF 55 SUNSCREEN STICK - DRUG FACTS LABEL

ACTIVE INGREDIENTS

AVOBENZONE 3.00%, HOMOSALATE 15.00%, OCTISALATE 5.00%, OCTOCRYLENE 10.00%, OXYBENZONE 6.00%

PURPOSE

SUNSCREEN

USES

- HELPS PREVENT SUNBURN
- HIGHER SPF GIVES MORE SUNBURN PROTECTION

WARNINGS:

FOR EXTERNAL USE ONLY

WHEN USING THIS PRODUCT:

- KEEP OUT OF THE EYES
- RINSE WITH WATER TO REMOVE

STOP USE AND ASK A DOCTOR IF RASH OR IRRITATION DEVELOPS OR LASTS

DIRECTIONS

- APPLY LIBERALLY 20 MINUTES BEFORE SUN EXPOSURE AND AS NEEDED
- FOR CHILDREN UNDER 6 MONTHS OF AGE, ASK A DOCTOR

SUN ALERT

Limiting sun exposure, wearing protective clothing and using sunscreen reduces the risk of skin aging, skin cancer and other harmful effects of the sun.

INACTIVE INGREDIENTS

BEESWAX, LAURYL LAURATE, OZOKERITE, CETEARYL BEHENATE, POLYBUTENE, CETYL ALCOHOL, STYRENE/ACRYLATES COPOLYMER, MYRISTYL MYRISTATE, TOCOPHEROL, COCOA SEED BUTTER, PHENOXYETHANOL, RETINYL PALMITATE, TETRAHEXYDECYL ASCORBATE

IMAGE OF LABEL

SPF55StickLabel.jpg